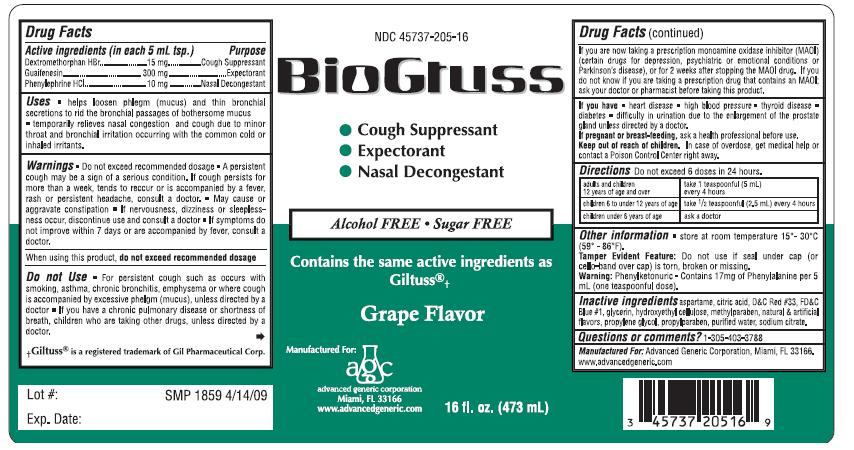 DRUG LABEL: BioGtuss
NDC: 45737-205 | Form: LIQUID
Manufacturer: Advanced Generic Corporation
Category: otc | Type: HUMAN OTC DRUG LABEL
Date: 20241220

ACTIVE INGREDIENTS: DEXTROMETHORPHAN HYDROBROMIDE 15 mg/5 mL; GUAIFENESIN 300 mg/5 mL; PHENYLEPHRINE HYDROCHLORIDE 15 mg/5 mL
INACTIVE INGREDIENTS: GLYCERIN; WATER; METHYLPARABEN; PROPYLPARABEN; PROPYLENE GLYCOL; SODIUM CITRATE; CITRIC ACID MONOHYDRATE; ASPARTAME; D&C RED NO. 33; FD&C BLUE NO. 1; HYDROXYMETHYL CELLULOSE

AGC-BioGTuss 205

Active Ingredients: (in each 5 mL tsp.) Purpose

Guaifenesin 300 mg .............................................. Expectorant
Dextromethorphan Hydrobromide 15 mg.................. Cough Suppressant
Phenylephrine HCl 10 mg.................................. Decongestant

Uses

- helps loosen phlegm (mucus) and thin bronchial secretions to rid the bronchial passages of bothersome mucus
- temporarily relieves nasal congestion and cough due to minor throat and bronchial irritation occurring with the common cold or inhaled irritants.

Warnings

- Do not exceed recommended dosage
- A persistent cough may be a sign of a serious condition. If cough persists for more than a week, tends to reoccur or is accompanied by a fever, rash or persistent headache, consult a doctor
- May cause or aggravate constipation
- If nervousness, dizziness or sleeplessness occur, discontinue use and consult a doctor
- If symptoms do not improve within 7 days or are accompanied by fever, consult a doctor.

Do not Use

- For persistent cough such as occurs with smoking, asthma, chronic bronchitis, emphysema or where cough is accompanied by excessive phelgm (mucus), unless directed by a doctor
- If you have a chronic pulmonary disease or shortness of breath, children who are taking other drugs, unless directed by a doctor. If you are now taking a prescription monoamine oxidase inhibitor (MAOI) (certain drugs for depression, psychiatric or emotional conditions or Parkinson’s disease), or for 2 weeks after stopping the MAOI drug. If you do not know if you are taking a prescription drug that contains an MAOI; ask your doctor or pharmacist before taking this product.

If you have

- heart disease
- high blood pressure
- thyroid disease
- diabetes
- difficulty in urination due to the enlargement of the prostate gland unless directed by a doctor.

Keep out of reach of children.

PREGNANCY OR BREAST FEEDING

If pregnant or breast-feeding,ask a health professional before use.

DOSAGE AND ADMINISTRATION

DirectionsDo not exceed 6 doses in 24 hours.
adults and children 12 years of age and over take 1 teaspoonful (5 mL) every 4 hours
children 6 to under 12 years of age take 1/2 teaspoonful (2.5 mL) every 4 hours

children under 6 years of age ask a doctor

Other information store at room temperature 15°- 30°C (59° - 86°F).
Tamper Evident Feature: Do not use if seal under cap (or cello-band over cap) is torn, broken or missing.

Warning:Phenylketonuric. Contains 17 mg of Phenylalanine per 5 mL (one teaspoonful dose).

INACTIVE INGREDIENT

Inactive Ingredients aspartame, citric acid, D and C Red No 33, FD and C Blue No 1, glycerine, hydroxymethyl cellulose, methylparaben, natural and artificial flavors, propylene glycol, propylparaben, purified water, sodium citrate

Questions or comments?1-305-403-3788

Manufactured For: Advanced Generic Corporation, Miami, Fl 33166

www.advancedgeneric.com